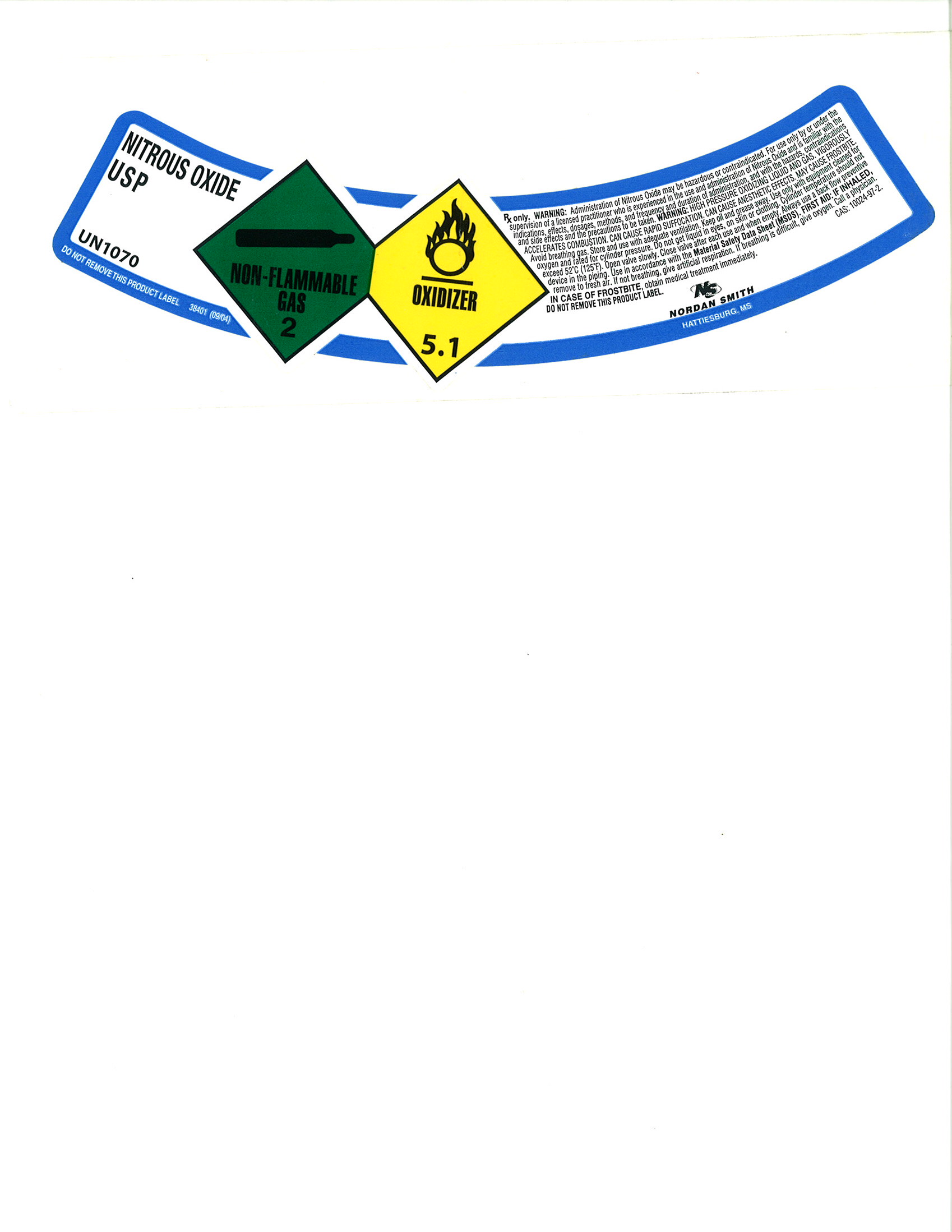 DRUG LABEL: Nitrous Oxide
NDC: 54416-006 | Form: GAS
Manufacturer: Nordan Smith Welding Supply
Category: prescription | Type: HUMAN PRESCRIPTION DRUG LABEL
Date: 20100909

ACTIVE INGREDIENTS: Nitrous Oxide 990 mL/1 L

Nitrous Oxide

PACKAGE LABEL

NITROUS OXIDE USP
UN1070
DO NOT REMOVE THIS PRODUCT LABEL
38401 (09/04)
NON-FLAMMBLE GAS / OXIDIZER
RX only. WARNING: Administration of Nitrous Oxide may be hazardous or contraindicated. For use only by or under the supervision of a licensed practitioner who is experienced in the use and administration of Nitrous Oxide and is familiar with the indications, effects, dosages, methods, and frequency and duration of administration, and with the hazards, contraindications and side effects and the precautions to be taken. WARNING: HIGH PRESSURE OXIDIZING LIQUID AND GAS. VIGOROUSLY ACCELERATES COMBUSTION. CAN CAUSE RAPID SUFFOCATION, CAN CAUSE ANESTHETIC EFFECTS. MAY CAUSE FRPSTBITE. Avoid breathing gas. Store and use with adequate ventilation. Keep oil and grease away. Use only with equipment cleaned for oxygen and rated for cylinder pressure. Do not get liquid in eyes, on skin or clothing. Cylinder temperature should not exceed 52° C (125°F). Open valve slowly. Close valve after each use and when empty. Always use a back flow preventive device in the piping. Use in accordance with the Material Safety Data Sheet (MSDS). FIRST AID: IF INHALED, remove to fresh air. If not breathing, give artificial respiration. If breathing is difficult, give oxygen. Call a physician. IN CASE OF FROSTBITE, obtain medical treatment immediately.
DO NOT REMOVE THIS PRODUCT LABEL.
N/S NORDAN SMITH HATTIESBURG, MS.
CAS: 10024-97-2.